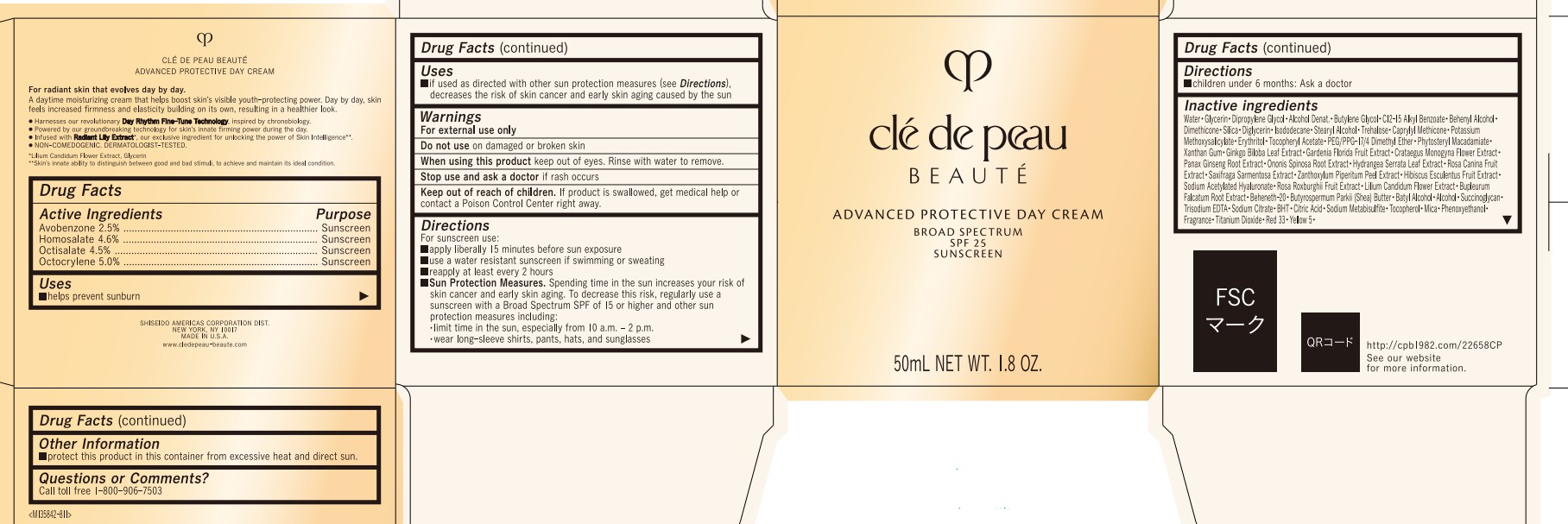 DRUG LABEL: cle de peau BEAUTE ADVANCED PROTECTIVE DAY
NDC: 58411-954 | Form: CREAM
Manufacturer: Shiseido Americas Corporation
Category: otc | Type: HUMAN OTC DRUG LABEL
Date: 20260223

ACTIVE INGREDIENTS: AVOBENZONE 1.2975 g/50 mL; HOMOSALATE 2.3874 g/50 mL; OCTISALATE 2.3175 g/50 mL; OCTOCRYLENE 2.595 g/50 mL
INACTIVE INGREDIENTS: WATER; GLYCERIN; ALCOHOL; BUTYLENE GLYCOL; C12-15 ALKYL BENZOATE; BEHENYL ALCOHOL; DIMETHICONE; SILICA; DIGLYCERIN; ISODODECANE; STEARYL ALCOHOL; TREHALOSE; CAPRYLYL METHICONE; POTASSIUM METHOXYSALICYLATE; ERYTHRITOL; .ALPHA.-TOCOPHEROL ACETATE; PEG/PPG-17/4 DIMETHYL ETHER; PHYTOSTERYL MACADAMIATE; XANTHAN GUM; GINKGO BILOBA LEAF; GARDENIA JASMINOIDES FRUIT; CRATAEGUS MONOGYNA FLOWER; PANAX GINSENG ROOT; ONONIS SPINOSA ROOT; HYDRANGEA SERRATA LEAF; ROSA CANINA FRUIT; SAXIFRAGA STOLONIFERA LEAF; ZANTHOXYLUM PIPERITUM FRUIT RIND; HIBISCUS ESCULENTUS SEED EXTRACT; SODIUM ACETYLATED HYALURONATE; ROSA ROXBURGHII FRUIT; LILIUM CANDIDUM FLOWER; BUPLEURUM FALCATUM ROOT; BEHENETH-20; SHEA BUTTER; BATYL ALCOHOL; SUCCINOGLYCAN (AGROBACTERIUM TUMEFACIENS); TRISODIUM EDTA; SODIUM CITRATE; BUTYLATED HYDROXYTOLUENE; CITRIC ACID; SODIUM METABISULFITE; TOCOPHEROL; MICA; PHENOXYETHANOL; TITANIUM DIOXIDE; D&C RED NO. 33; FD&C YELLOW NO. 5

cle de peau BEAUTE ADVANCED PROTECTIVE DAY

Drug Facts

Active Ingredients | Purpose
Avobenzone 2.5% | Sunscreen
Homosalate 4.6% | Sunscreen
Octisalate 4.5% | Sunscreen
Octocrylene 5.0% | Sunscreen

Uses

- helps prevent sunburn
- if used as directed with other sun protection measures (see Directions), decreases the risk of skin cancer and early skin aging caused by the sun

Warnings

For external use only

Do not useon damaged or broken skin

When using this product keep out of eyes. Rinse with water to remove.

Stop use and ask a doctor if rash occurs

Keep out of reach of children. If product is swallowed, get medical help or contact a Poison Control Center right away.

Directions

For sunscreen use:

- apply liberally 15 minutes before sun exposure
- use a water resistant sunscreen if swimming or sweating
- reapply at least every 2 hours
- Sun Protection Measures. Spending time in the sun increases your risk of skin cancer and early skin aging. To decrease this risk, regularly use a sunscreen with a Broad Spectrum SPF of 15 or higher and other sun protection measures including:

• limit time in the sun, especially from 10 a.m. - 2 p.m.

• wear long-sleeves shirts, pants, hats, and sunglasses

- children under 6 months: Ask a doctor

INACTIVE INGREDIENT

WATER･GLYCERIN･DIPROPYLENE GLYCOL･ALCOHOL DENAT.･BUTYLENE GLYCOL･C12-15 ALKYL BENZOATE･BEHENYL ALCOHOL･DIMETHICONE･SILICA･DIGLYCERIN･ISODODECANE･STEARYL ALCOHOL･TREHALOSE･CAPRYLYL METHICONE･POTASSIUM METHOXYSALICYLATE･ERYTHRITOL･TOCOPHERYL ACETATE･PEG/PPG-17/4 DIMETHYL ETHER･PHYTOSTERYL MACADAMIATE･XANTHAN GUM･GINKGO BILOBA LEAF EXTRACT･GARDENIA FLORIDA FRUIT EXTRACT･CRATAEGUS MONOGYNA FLOWER EXTRACT･PANAX GINSENG ROOT EXTRACT･ONONIS SPINOSA ROOT EXTRACT･HYDRANGEA SERRATA LEAF EXTRACT･ROSA CANINA FRUIT EXTRACT･SAXIFRAGA SARMENTOSA EXTRACT･ZANTHOXYLUM PIPERITUM PEEL EXTRACT･HIBISCUS ESCULENTUS FRUIT EXTRACT･SODIUM ACETYLATED HYALURONATE･ROSA ROXBURGHII FRUIT EXTRACT･LILIUM CANDIDUM FLOWER EXTRACT･BUPLEURUM FALCATUM ROOT EXTRACT･BEHENETH-20･BUTYROSPERMUM PARKII (SHEA) BUTTER･BATYL ALCOHOL･ALCOHOL･SUCCINOGLYCAN･TRISODIUM EDTA･SODIUM CITRATE･BHT･CITRIC ACID･SODIUM METABISULFITE･TOCOPHEROL･MICA･PHENOXYETHANOL･FRAGRANCE･TITANIUM DIOXIDE･RED 33･YELLOW 5･

Other information

- protect this product in this container from excessibe heat and direct sunlight

Questions or Comments?

Call toll free 1-800-906-7503

PRINCIPAL DISPLAY PANNEL - 50 mL Jar Carton

clé de peau

BEAUTÉ

ADVANCED PROTECTIVE DAY CREAM

BROAD SPECTRUM

SPF 25

SUNSCREEN

50mL NET WT. 1.8 OZ.